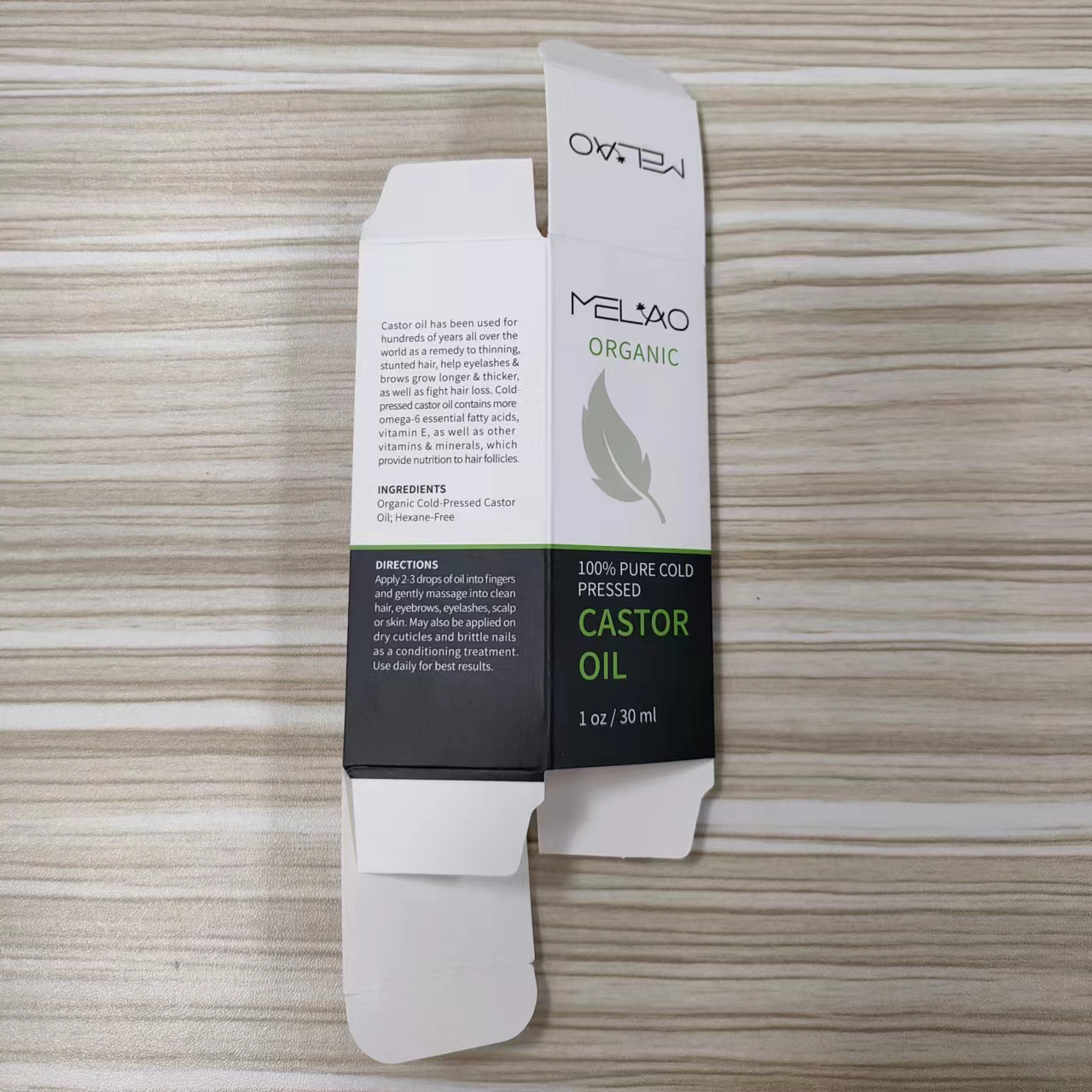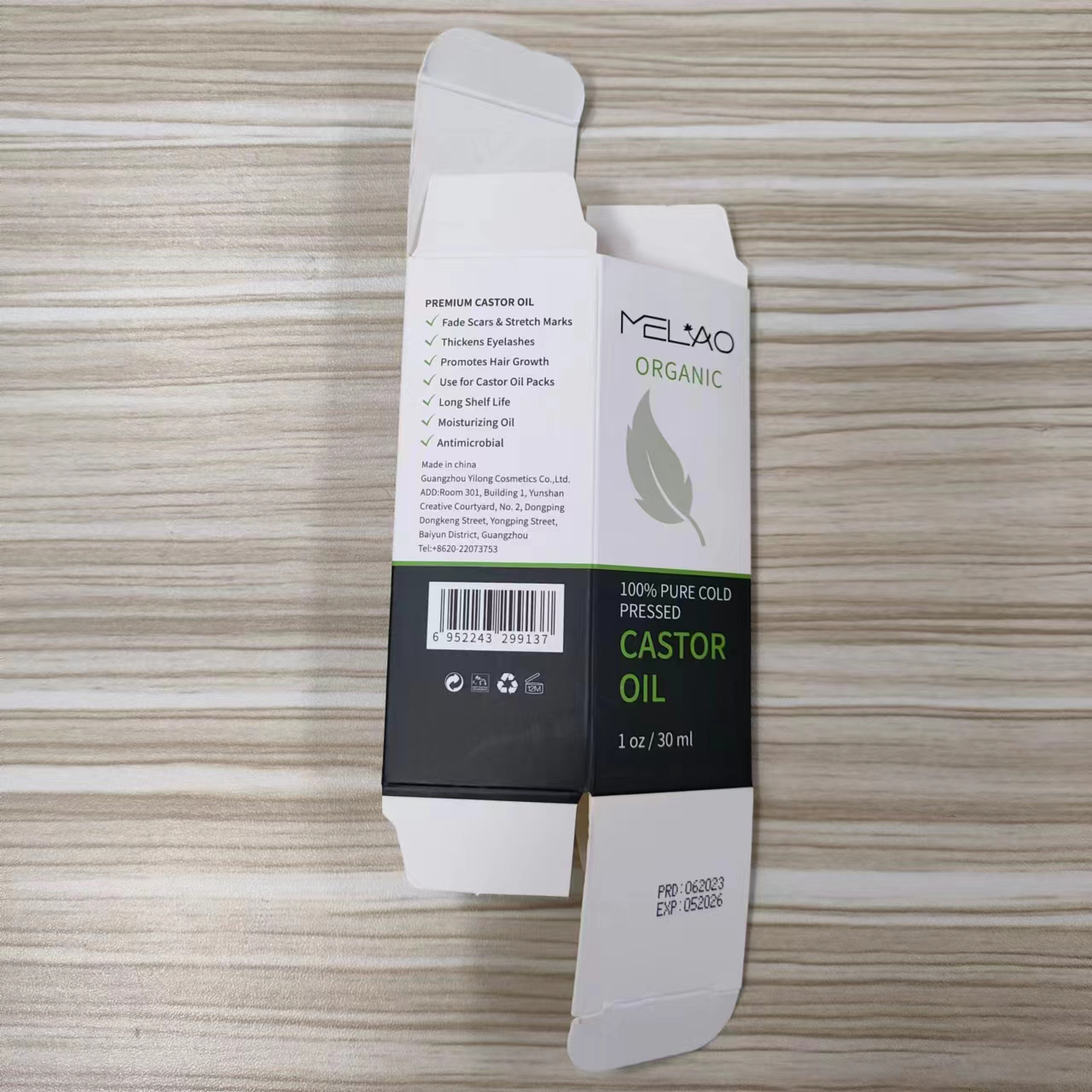 DRUG LABEL: MELAO castor oil
NDC: 83566-043 | Form: OIL
Manufacturer: Guangzhou Yilong Cosmetics Co.,Ltd.
Category: otc | Type: HUMAN OTC DRUG LABEL
Date: 20240604

ACTIVE INGREDIENTS: RICINUS COMMUNIS SEED 100 g/30 mL
INACTIVE INGREDIENTS: WATER

MELAO CASTOR OIL

ACTIVE INGREDIENT

Ricinus Communis (Castor) Seed Oil

PURPOSE

1.Fade Scars & Stretch Marks.

2.Thickens Eyelashes.

3.Promotes Hair Growth.

4.Moisturizing Oil.

INDICATIONS AND USAGE

Apply 2-3 drops of oil into fingers and gently massage into clean hair,eyebrows, eyelashes, scalp or skin. May also be applied on dry cuticles and brittle nails as a conditioning treatment.Use daily for best results.

WARNINGS

For external use only.

Stop use and ask a doctor if rash occurs.

Do not use on damaged or broken skin.

When using this product keep out of eyes. Rinse with water to remove.

Keep out of reach of children. If swallowed, get medical help or contact a Poison Control Center right away.

DOSAGE AND ADMINISTRATION

Before first use, apply 1-2 drops behind the ear and observe for any allergic reaction.
Take 1-2 pumps per use and apply evenly to dry hair ends, skin and other areas of need.

INACTIVE INGREDIENT

water